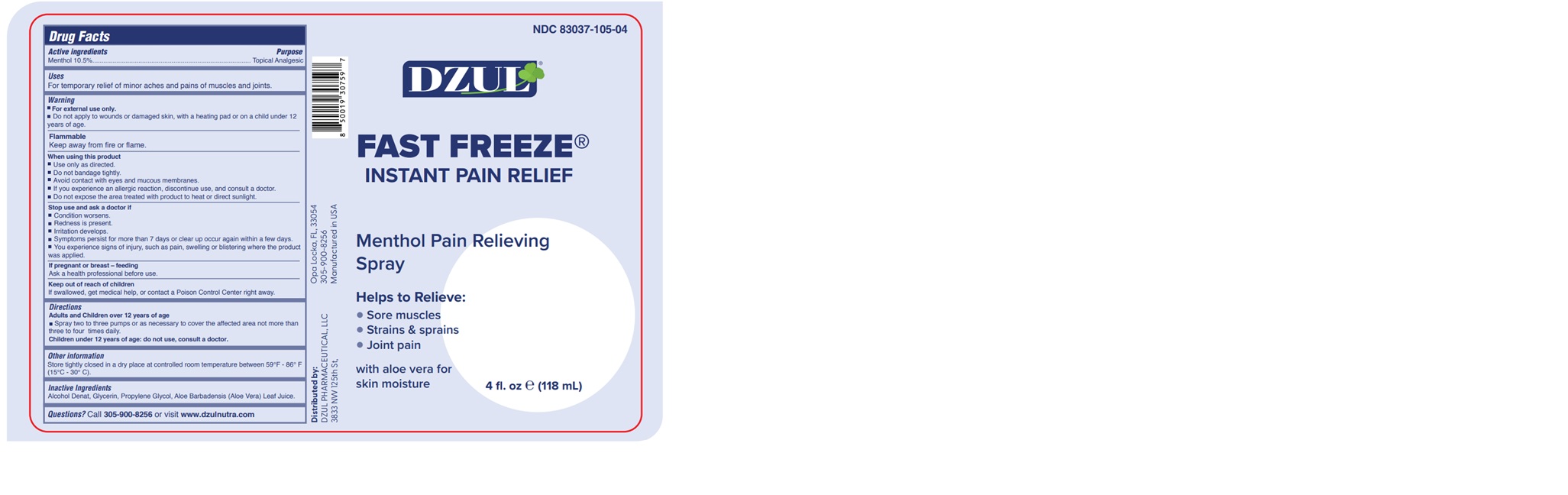 DRUG LABEL: DZUL FAST FREEZE
NDC: 83037-105 | Form: SPRAY
Manufacturer: Caball Sales, Inc.
Category: otc | Type: HUMAN OTC DRUG LABEL
Date: 20250617

ACTIVE INGREDIENTS: MENTHOL 9 g/100 mL
INACTIVE INGREDIENTS: ALCOHOL; PROPYLENE GLYCOL; GLYCERIN; ALOE BARBADENSIS LEAF JUICE

83037-105-04

ACTIVE INGREDIENT

Menthol 10.5%

PURPOSE

Topical Analgesic

USE

For temporary relief of minor aches and pains of muscles and joints.

WARNINGS

For external use only.

Do not apply to wounds or damaged skin, with a heating pad or on a child under 12 years of age.

Flammable

Keep away from fire or flame.

WHEN USING

Use only as directed.
Do not bandage tightly.
Avoid contact with eyes and mucous membranes.
If you experience an allergic reaction, discontinue use, and consult a doctor.

Do not expose the area treated with product to heat or direct sunlight.

Stop use and ask a doctor if

Condition worsens.
Redness is present.
Irritation develops.
Symptoms persist for more than 7 days or clear up occur again within a few days.

You experience signs of injury, such as pain, swelling or blistering where the product was applied.

If pregnant or breast – feeding

Ask a health professional before use.

KEEP OUT OF REACH OF CHILDREN

If swallowed, get medical help, or contact a Poison Control Center right away.

DIRECTIONS

Adults and Children over 12 years of age

Spray two to three pumps or as necessary to cover the affected area not more than three to four times daily.

Children under 12 years of age: do not use, consult a doctor.

OTHER INFORMATION

Store tightly closed in a dry place at controlled room temperature between 59-86 F (15°-30° C).

INACTIVE INGREDIENT

Alcohol Denat, Glycerin, Propylene Glycol, Aloe Barbadensis (Aloe Vera) Leaf Juice.